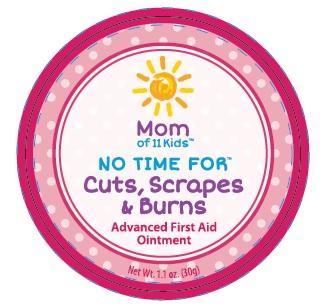 DRUG LABEL: Mom of 11 Kids No Time For Cuts, Scrapes and Burns
NDC: 24909-509 | Form: OINTMENT
Manufacturer: Aidance Skincare & Topical Solutions, LLC
Category: homeopathic | Type: HUMAN OTC DRUG LABEL
Date: 20150820

ACTIVE INGREDIENTS: CALENDULA OFFICINALIS FLOWER 6 [hp_X]/100 g
INACTIVE INGREDIENTS: CHAMOMILE FLOWER OIL; COTTONSEED OIL; JOJOBA OIL; GARCINIA INDICA FRUIT; MAGNESIUM OXIDE; SILVER OXIDE; WHITE WAX; ZINC OXIDE

Drug Facts

Active Ingredients

Calendula 1X HPUS

Purpose

Calendula - Healing agent

Uses

Promotes healing from minor cuts, scrapes, burns and skin irritations.

Warnings

For external use only. Stop use and ask a doctor if condition worsens or if symptoms persist for more than 7 days, or clear up and occur again within a few days. When using this product avoid contact with eyes.

Keep out of reach of children.

If swallowed, get medical help or contact a Poison Control Center right away.

Directions

Apply a thin layer to clean, dry skin up to 3 times daily. Cover with sterile bandage. Continue until skin improves.

Inactive Ingredients

Beeswax (organic), Chamomile Oil, Cotton Seed Oil, Jojoba Seed Oil (golden), Kokum Butter, Magnesium Oxide, Silver Oxide, Zinc Oxide.

PRINCIPAL DISPLAY PANEL - 30g Label

Mom of 11 Kids™
NO TIME FOR™
Cuts, Scrapes & Burns
Advanced First Aid Ointment
Safe & Natural is Finally Fast & Effective™
Net Wt. 1.1 oz. (30g)